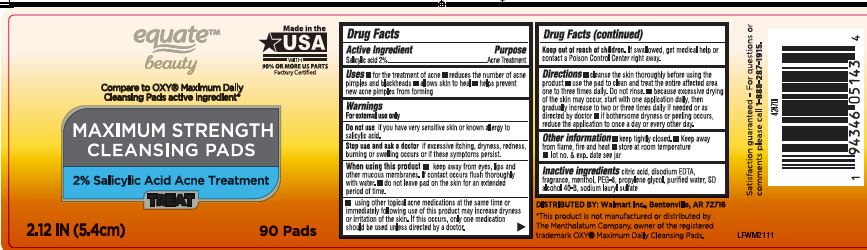 DRUG LABEL: Maximum Sterngth Cleansing Pads

NDC: 79903-207 | Form: LIQUID
Manufacturer: Walmart
Category: otc | Type: HUMAN OTC DRUG LABEL
Date: 20240311

ACTIVE INGREDIENTS: SALICYLIC ACID 2 g/1 1
INACTIVE INGREDIENTS: CITRIC ACID MONOHYDRATE; EDETATE DISODIUM ANHYDROUS; MENTHOL; POLYETHYLENE GLYCOL 400; PROPYLENE GLYCOL; WATER; ALCOHOL; SODIUM LAURYL SULFATE

Active Ingredient Purpose

Salicylic Acid 2%...................Acne Treatment

Uses

for the treatment of acne • reduces the number of acne pimples and blackheads • allows skin to heal • helps prevent new acne pimples from forming

Warnings

For external use only

Do not use

if you have very sensitive skin or known allergy to salicylic acid

Stop use and ask a doctor ifexcessive itching, dryness, redness, burning or swelling occurs or if these symptoms persist

When using this product

keep away from eyes,lips, other mucous membranes. If contact occurs flush thoroughly with water • do not leave pad on skin for an extended period of time

Using other topical acne medications at the same time or immediately following use of this product may increase dryness or irritation of the skin. If this occurs, only one medication should be used unless directed by a doctor.

Keep out of reach of children.

If swallowed, get medical help or contact a Poison Control Center right away.

Directions

cleanse the skin thoroughly before using the product • use the pad to clean and treat the entire affected area one to three times daily. Do not rinse. • because excessive drying of the skin may occur, start with one application daily, then gradually increase to two or three times daily if needed or as directed by doctor • if bothersome dryness or peeling occurs, reduce the application to once a day or every other day

Inactive ingredients

citric acid, disodium EDTA, fragrance, menthol, PEG-8, propylene glycol, purified water, SD alcohol 40-B, sodium lauryl sulfate